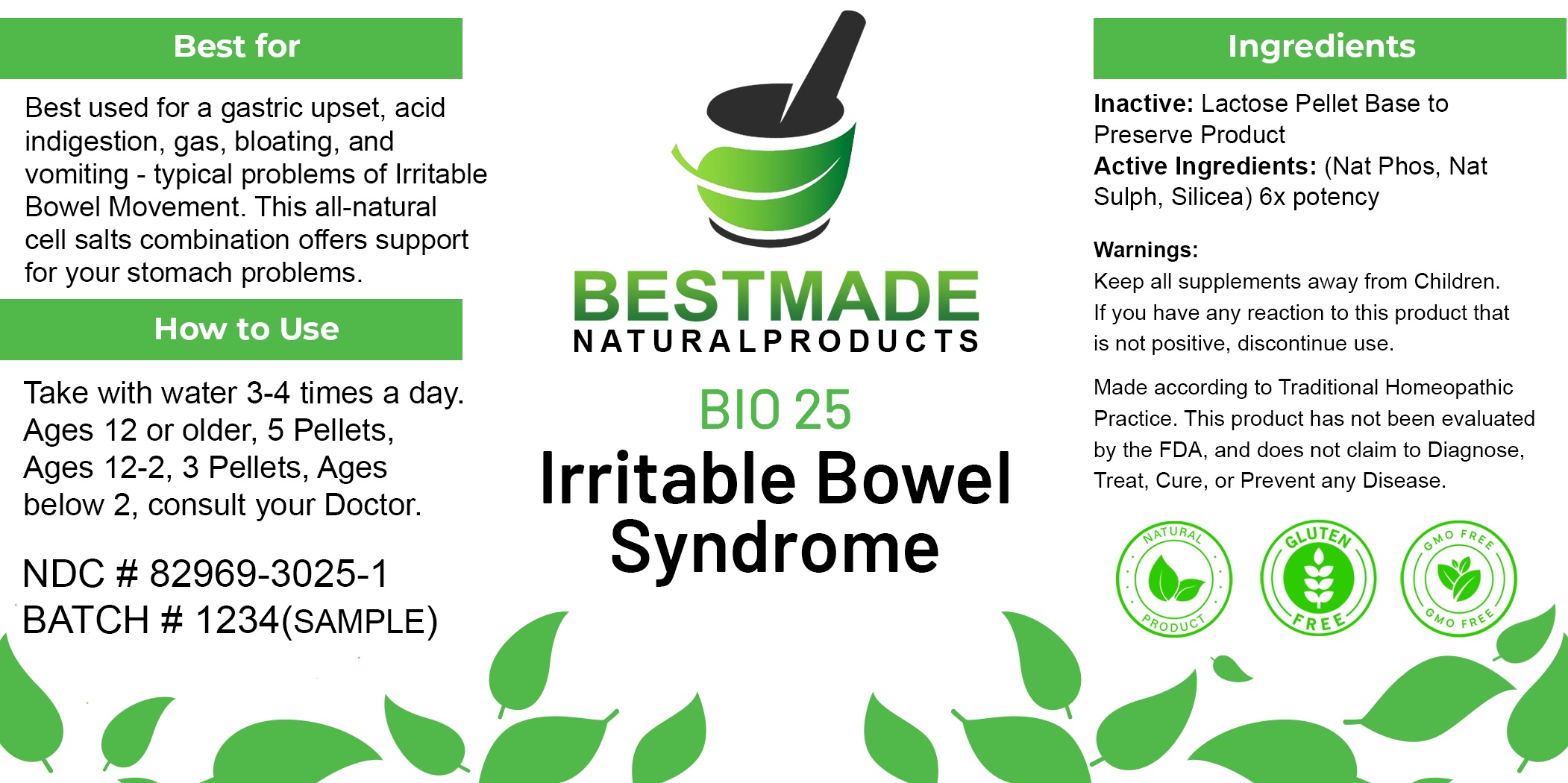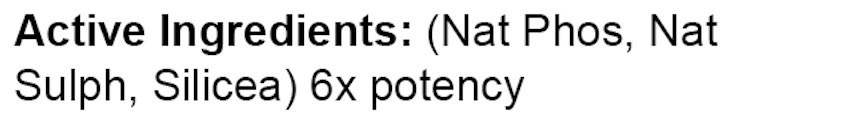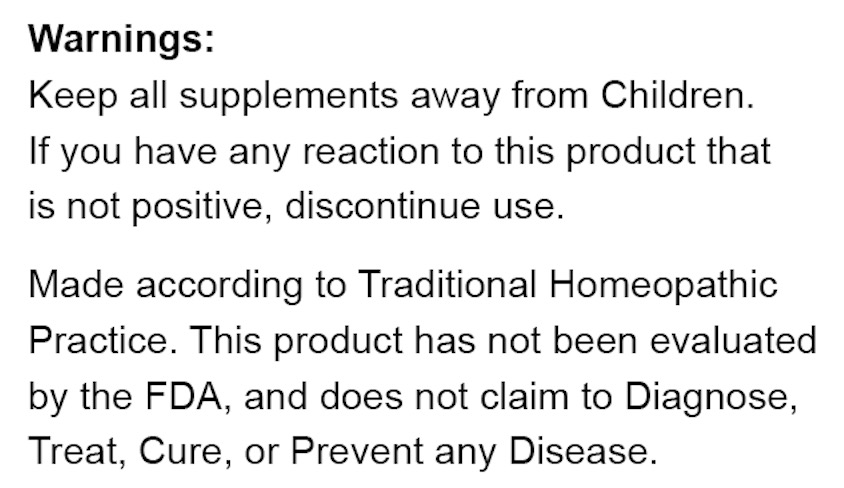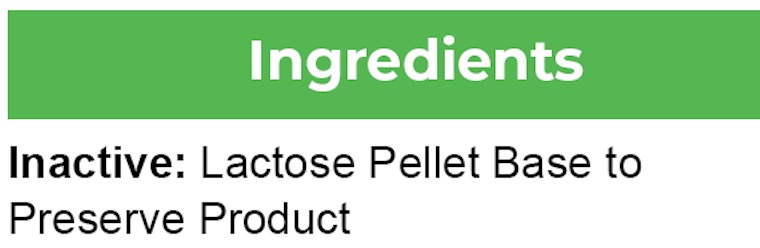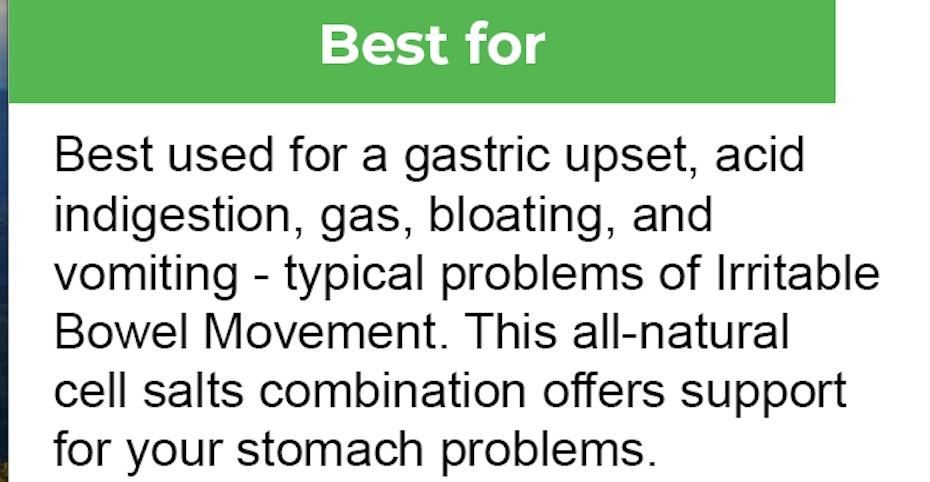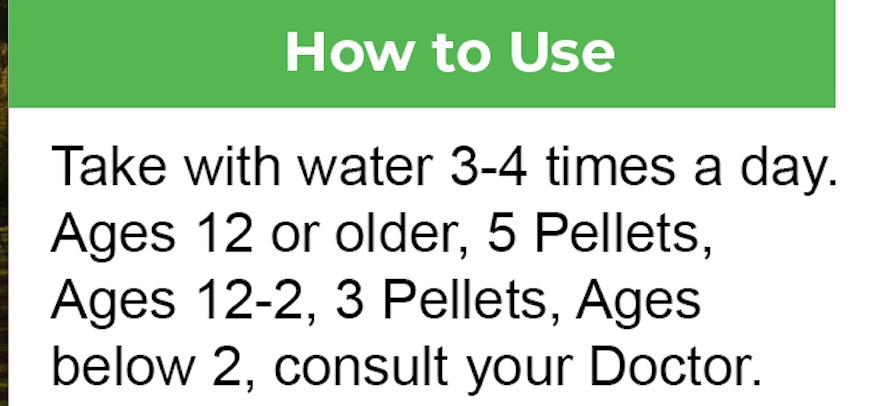 DRUG LABEL: Bestmade Natural Products Bio25
NDC: 82969-3025 | Form: TABLET, SOLUBLE
Manufacturer: Bestmade Natural Products
Category: homeopathic | Type: HUMAN OTC DRUG LABEL
Date: 20241217

ACTIVE INGREDIENTS: SILICON DIOXIDE 6 [hp_X]/6 [hp_X]; SODIUM PHOSPHATE, DIBASIC, HEPTAHYDRATE 6 [hp_X]/6 [hp_X]; SODIUM SULFATE 6 [hp_X]/6 [hp_X]
INACTIVE INGREDIENTS: LACTOSE, UNSPECIFIED FORM 6 [hp_X]/6 [hp_X]

bio25

DOSAGE AND ADMINISTRATION

How to Use
Take with water 3-4 times a day.
Ages 12 or older, 5 Pellets,
Ages 12-2, 3 Pellets, Ages
below 2, consult your Doctor.

INACTIVE INGREDIENT

Using a blank lactose pellet base to preserve and package product.

INDICATIONS AND USAGE

Best used for a gastric upset, acid indigestion, gas, bloating, and vomiting - typical problems of Irritable Bowel Movement. This all-natural cell salts combination offers support for your stomach problems.

ACTIVE INGREDIENT

(Nat Phos, Nat Sulf, Silicea) 6x

Keep out of reach of children.

PURPOSE

Best used for gastric upset, acid indigestion, gas, bloating, and vomiting - typical problems of Irritable Bowel Movement. This all-natural cell salts combination offers support for your stomach problems.

Warnings:
Keep all supplements away from Children.
If you have any reaction to this product that is not positive, discontinue use.

Made according to Traditional Homeopathic Practice. This product has not been evaluated by the FDA, and does not claim to Diagnose, Treat, Cure, or Prevent any Disease.

RECENT MAJOR CHANGES

Package label redesigned.

Entire Package label